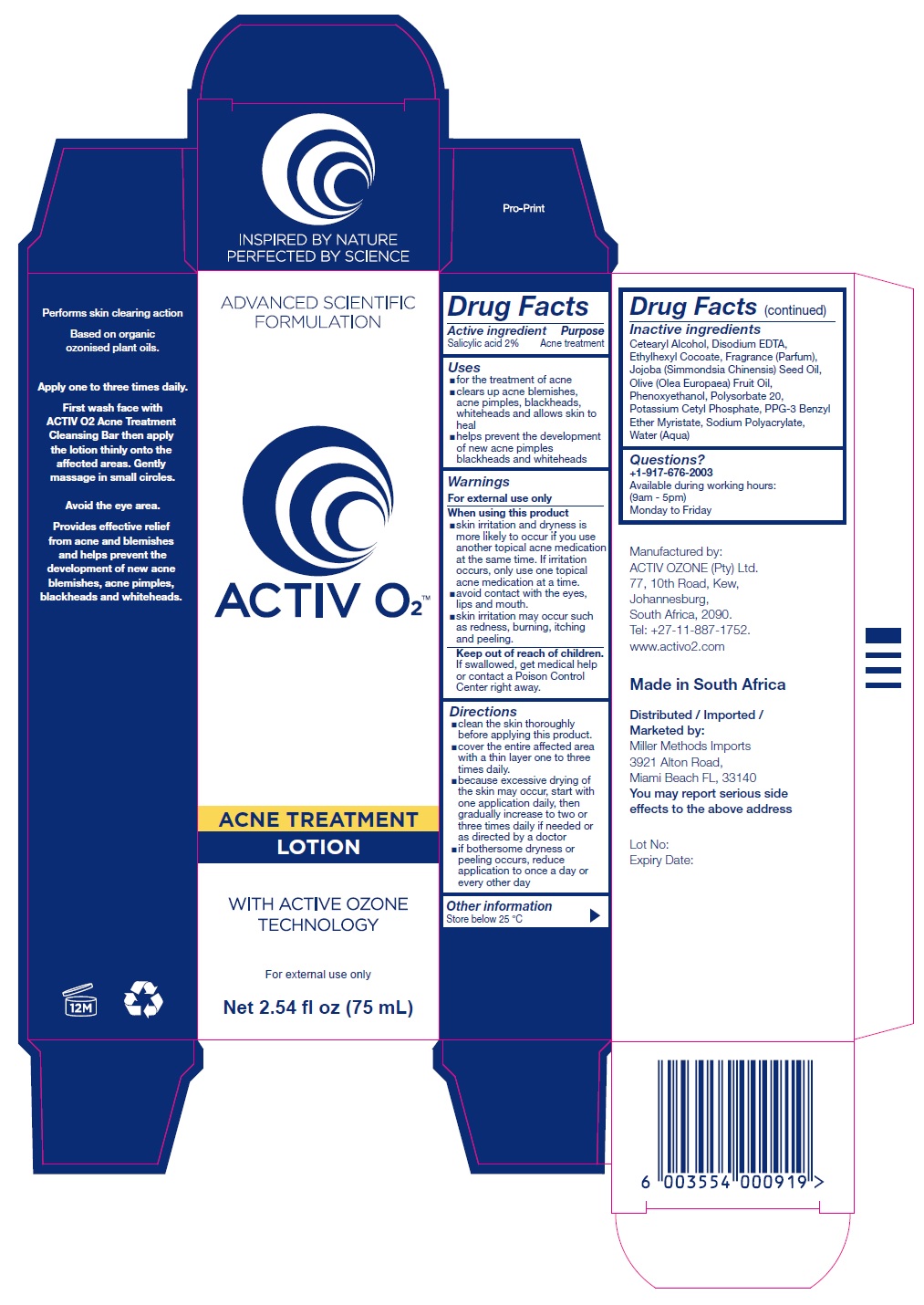 DRUG LABEL: Activ O2 Acne Treatment
NDC: 71577-333 | Form: LOTION
Manufacturer: Activ Ozone (pty) Ltd
Category: otc | Type: HUMAN OTC DRUG LABEL
Date: 20170918

ACTIVE INGREDIENTS: SALICYLIC ACID 2 g/100 mL
INACTIVE INGREDIENTS: CETOSTEARYL ALCOHOL; EDETATE DISODIUM ANHYDROUS; ETHYLHEXYL COCOATE; JOJOBA OIL; OLIVE OIL; PHENOXYETHANOL; POLYSORBATE 20; POTASSIUM CETYL PHOSPHATE; PPG-3 BENZYL ETHER MYRISTATE; SODIUM POLYACRYLATE (8000 MW); WATER

ACTIV O2 ACNE TREATMENT LOTION

Active ingredient

Salicylic acid 2%

Purpose

Acne treatment

Uses

- for the treatment of acne
- clears up acne blemishes, acne pimples, blackheads, whiteheads and allows skin to heal
- helps prevent the development of new acne pimples blackheads and whiteheads

Warnings

For external use only

When using this product

- skin irritation and dryness is more likely to occur if you use another topical acne medication at the same time. If irritation occurs, only use one topical acne medication at a time.
- avoid contact with the eyes, lips and mouth.
- skin irritation may occur such as redness, burning, itching and peeling.

Keep out of reach of children. If swallowed, get medical help or contact a Poison Control Center right away.

Directions

- clean the skin thoroughly before applying this product.
- cover the entire affected area with a thin layer one to three times daily.
- because excessive drying of the skin may occur, start with one application daily, then gradually increase to two or three times daily if needed or as directed by a doctor
- if bothersome dryness or peeling occurs, reduce application to once a day or every other day

Inactive ingredients

Cetearyl Alcohol, Disodium EDTA, Ethylhexyl Cocoate, Fragrance (Parfum), Jojoba (Simmondsia Chinensis) Seed Oil, Olive (Olea Europaea) Fruit Oil, Phenoxyethanol, Polysorbate 20, Potassium Cetyl Phosphate, PPG-3 Benzyl Ether Myristate, Sodium Polyacrylate, Water (Aqua)

Other information

Store below 25 °C

Questions?

+1-917-676-2003

Available during working hours:

(9am - 5pm)

Monday to Friday

Manufactured by:

ACTIV OZONE (Pty) Ltd.

77, 10th Road, Kew,

Johannesburg,

South Africa, 2090.

Tel: +27-11-887-1752

www.activo2.com

Made in South Africa

Distributed / Imported / Marketed by:

Miller Methods Imports

3921 Alton Road,

Miami Beach FL, 33140

You may report serious side effects to the above address

INSPIRED BY NATURE

PERFECTED BY SCIENCE

ADVANCED SCIENTIFIC FORMULATION

WITH ACTIVE OZONE TECHNOLOGY

Performs skin clearing action

Based on organic ozonised plant oils.

Apply one to three times daily.

First wash face with ACTIV O2 Acne Treatment Cleansing Bar then apply the lotion thinly onto the affected areas. Gently massage in small circles.

Avoid the eye area.

Provides effective relief from acne and blemishes and helps prevent the development of new acne blemishes, acne pimples, blackheads and whiteheads.